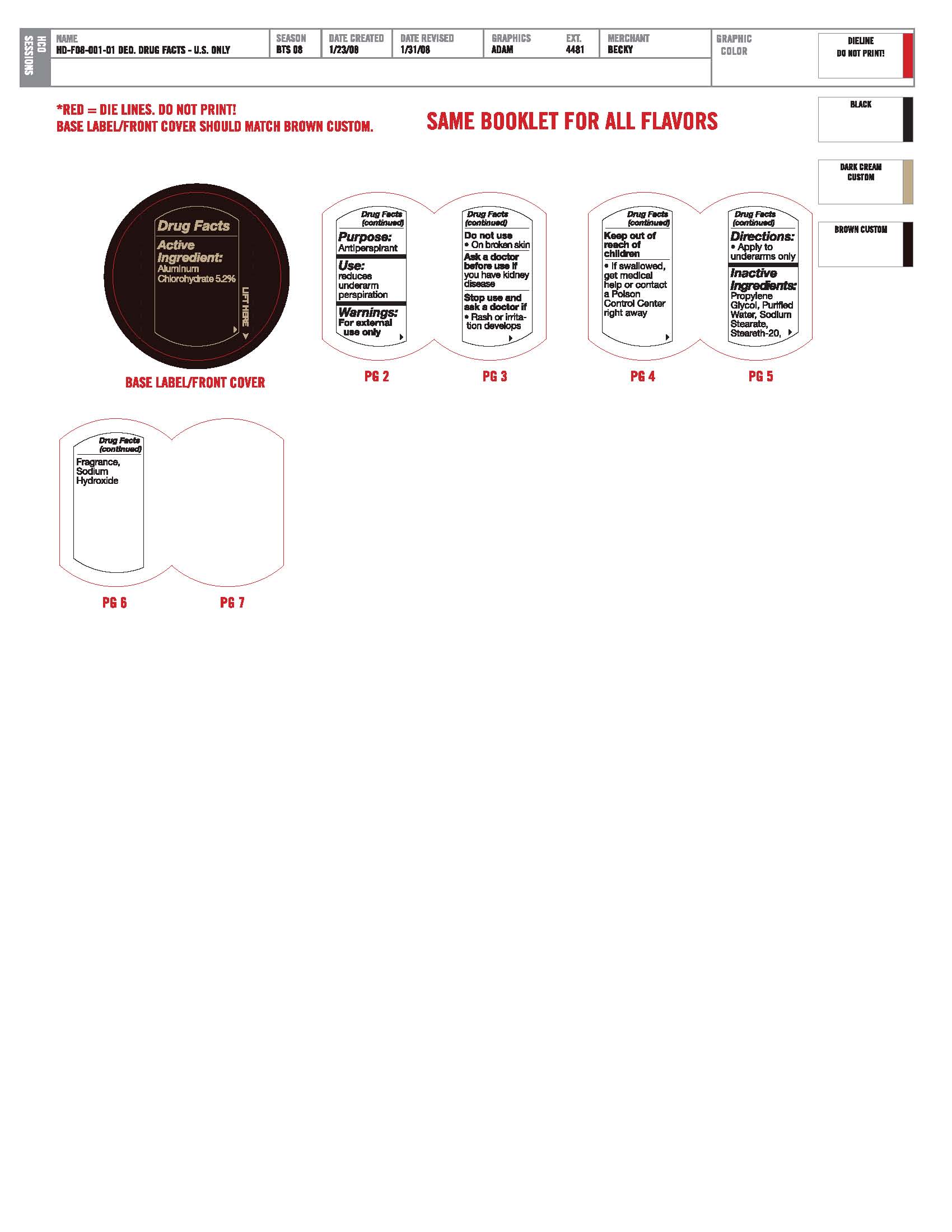 DRUG LABEL: Anti-Perspirant Deodorant
NDC: 57367-008 | Form: STICK
Manufacturer: 220 Laboratories Inc
Category: otc | Type: HUMAN OTC DRUG LABEL
Date: 20100525

ACTIVE INGREDIENTS: ALUMINUM CHLOROHYDRATE 52 mg/1 g
INACTIVE INGREDIENTS: PROPYLENE GLYCOL; WATER; SODIUM STEARATE; STEARETH-20; SODIUM HYDROXIDE

Anti-Perspirant Deodorant Artwork

PURPOSE

Use: Reduces underarm perspiration.

DOSAGE AND ADMINISTRATION

Directions: Apply to underarms only.

WARNINGS

Warnings: For external use only. Keep out of reach of children.

Active Ingredients: Aluminum Chlorohydrate 5.2%.

INACTIVE INGREDIENT

Inactive Ingredients: Propylene Glycol, Purified Water, Sodium Stearate, Steareth-20, Fragrance, Sodium Hydroxide.